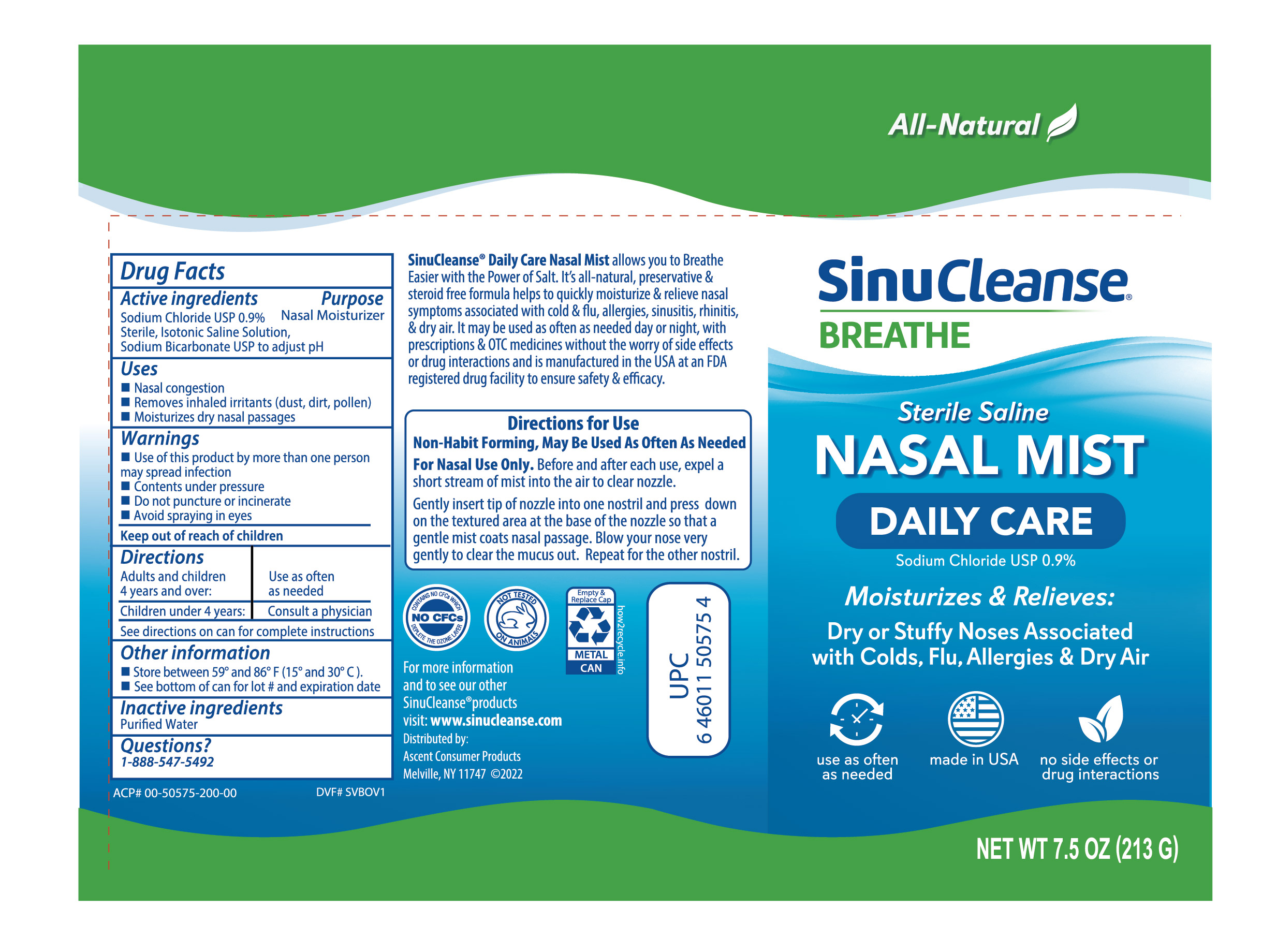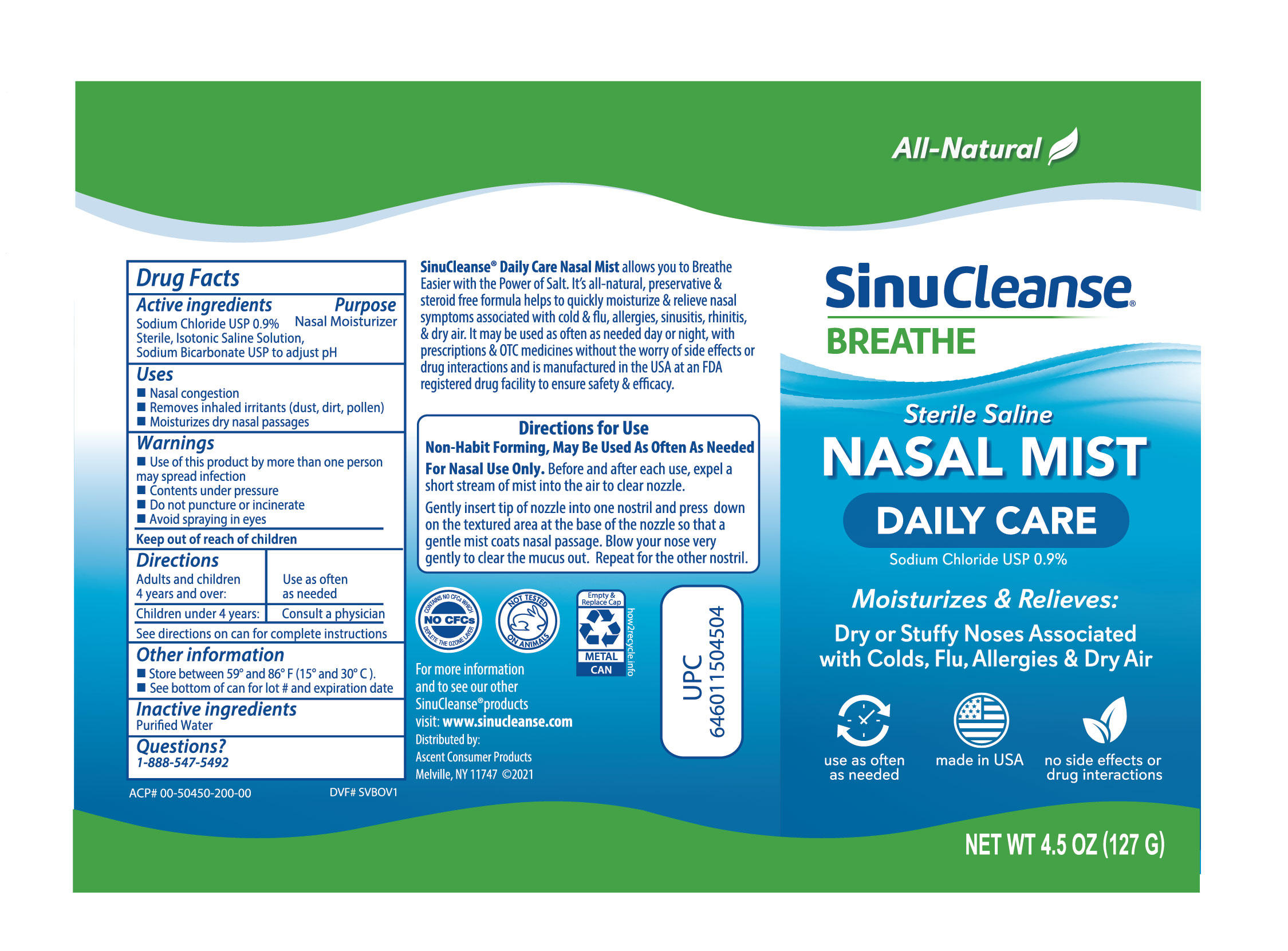 DRUG LABEL: SinuCleanse Sterile Saline Mist Daily Care
NDC: 42829-504 | Form: SPRAY
Manufacturer: ASCENT CONSUMER PRODUCTS, INC
Category: otc | Type: HUMAN OTC DRUG LABEL
Date: 20220108

ACTIVE INGREDIENTS: SODIUM CHLORIDE 0.9 g/100 g
INACTIVE INGREDIENTS: WATER

SinuCleanse Sterile Nasal Saline Mist- Daily Care

Active Ingredient

Sodium Chloride 0.9%

Sterile, Isotonic Saline Solution,

Sodium Bicarbonate USP to adjust pH

Purpose

Nasal Moisturizer

Uses

- Nasal congestion
- Removes inhaled irritants (dust, dirt, pollen)
- Moisturizes dry nasal passages

Directions

Adults and children 4 years and over: Use as often as needed
Children under 4 years: Consult a physician
See directions on can for complete instructions

Warnings

Use of this product by more than one person may spread infection
Contents under pressure
Do not puncture or incinerate
Avoid spraying in eyes

Other Information

Store between 59 and 86 degree F

Inactive ingredients

Purfied Water

QUESTIONS ?

1-888-547-5492